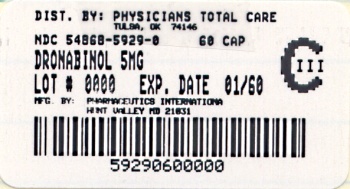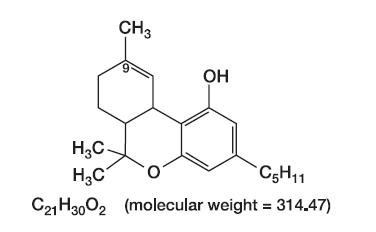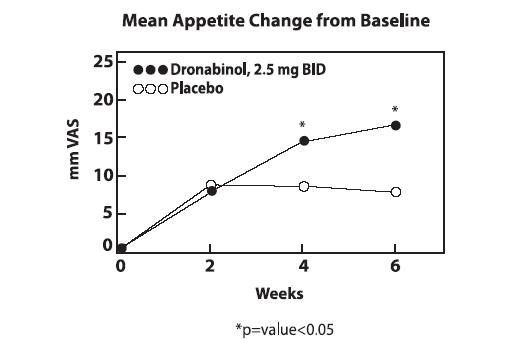 DRUG LABEL: Dronabinol
                        
NDC: 54868-5929 | Form: CAPSULE
Manufacturer: Physicians Total Care, Inc.
Category: prescription | Type: HUMAN PRESCRIPTION DRUG LABEL
Date: 20120127
DEA Schedule: CIII

ACTIVE INGREDIENTS: DRONABINOL 5 mg/1 1
INACTIVE INGREDIENTS: FD&C YELLOW NO. 6; GELATIN; GLYCERIN; WATER; SESAME OIL; TITANIUM DIOXIDE; FD&C BLUE NO. 1; FD&C RED NO. 40; FERROSOFERRIC OXIDE; SHELLAC; ISOPROPYL ALCOHOL; BUTYL ALCOHOL; PROPYLENE GLYCOL; AMMONIA

Dronabinol Capsules, USP
CIII
Rx only

DESCRIPTION

Dronabinol is a cannabinoid designated chemically as (6aR-trans)-6a,7,8,10a-tetrahydro-6,6,9-trimethyl-3-pentyl-6H-dibenzo[b,d]pyran-1-ol. Dronabinol has the following molecular and structural formulas:

Dronabinol, the active ingredient in dronabinol capsules, is synthetic delta-9-tetrahydrocannabinol (delta-9-THC). Delta-9-tetrahydrocannabinol is also a naturally occurring component of Cannabis sativa L. (Marijuana).

Dronabinol is a light yellow resinous oil that is sticky at room temperature and hardens upon refrigeration. Dronabinol is insoluble in water and is formulated in sesame oil. It has a pKa of 10.6 and an octanol-water partition coefficient: 6,000:1 at pH 7.

Capsules for oral administration: Dronabinol capsules are supplied as oblong, soft gelatin capsules containing 2.5 mg, 5 mg or 10 mg dronabinol. Each dronabinol capsule strength is formulated with the following inactive ingredients: FD&C Yellow No. 6, gelatin, glycerin, purified water, sesame oil, titanium dioxide, iron oxide black, shellac glaze, isopropyl alcohol, n-butyl alcohol, propylene glycol, and ammonium hydroxide. The 2.5 mg and 5 mg also contain FD&C Blue No. 1 and FD&C Red No. 40.

CLINICAL PHARMACOLOGY

Dronabinol is an orally active cannabinoid which, like other cannabinoids, has complex effects on the central nervous system (CNS), including central sympathomimetic activity. Cannabinoid receptors have been discovered in neural tissues. These receptors may play a role in mediating the effects of dronabinol and other cannabinoids.

Pharmacodynamics

Dronabinol-induced sympathomimetic activity may result in tachycardia and/or conjunctival injection. Its effects on blood pressure are inconsistent, but occasional subjects have experienced orthostatic hypotension and/or syncope upon abrupt standing.

Dronabinol also demonstrates reversible effects on appetite, mood, cognition, memory, and perception. These phenomena appear to be dose-related, increasing in frequency with higher dosages, and subject to great interpatient variability.

After oral administration, dronabinol has an onset of action of approximately 0.5 to 1 hours and peak effect at 2 to 4 hours. Duration of action for psychoactive effects is 4 to 6 hours, but the appetite stimulant effect of dronabinol may continue for 24 hours or longer after administration.

Tachyphylaxis and tolerance develop to some of the pharmacologic effects of dronabinol and other cannabinoids with chronic use, suggesting an indirect effect on sympathetic neurons. In a study of the pharmacodynamics of chronic dronabinol exposure, healthy male volunteers (N = 12) received 210 mg/day dronabinol, administered orally in divided doses, for 16 days. An initial tachycardia induced by dronabinol was replaced successively by normal sinus rhythm and then bradycardia. A decrease in supine blood pressure, made worse by standing, was also observed initially. These volunteers developed tolerance to the cardiovascular and subjective adverse CNS effects of dronabinol within 12 days of treatment initiation.

Tachyphylaxis and tolerance do not, however, appear to develop to the appetite stimulant effect of dronabinol capsules. In studies involving patients with Acquired Immune Deficiency Syndrome (AIDS), the appetite stimulant effect of dronabinol capsules has been sustained for up to five months in clinical trials, at dosages ranging from 2.5 mg/day to 20 mg/day.

Pharmacokinetics

Absorption and Distribution: Dronabinol capsules are almost completely absorbed (90 to 95%) after single oral doses. Due to the combined effects of first pass hepatic metabolism and high lipid solubility, only 10 to 20% of the administered dose reaches the systemic circulation. Dronabinol has a large apparent volume of distribution, approximately 10 L/kg, because of its lipid solubility. The plasma protein binding of dronabinol and its metabolites is approximately 97%.

The elimination phase of dronabinol can be described using a two compartment model with an initial (alpha) half-life of about 4 hours and a terminal (beta) half-life of 25 to 36 hours. Because of its large volume of distribution, dronabinol and its metabolites may be excreted at low levels for prolonged periods of time.

The pharmacokinetics of dronabinol after single doses (2.5, 5, and 10 mg) and multiple doses (2.5, 5, and 10 mg given twice a day; BID) have been studied in healthy women and men.

Summary of Multiple-Dose Pharmacokinetic Parameters of Dronabinol in Healthy Volunteers (n=34; 20-45 years) under Fasted Conditions
Mean (SD) PK Parameter Values
BID Dose | Cmax ng/mL | Median Tmax (range, hr | AUC (0-12) ng●hr/mL
2.5 mg | 1.32 (0.62) | 1.00 (0.50-4.00) | 2.88 (1.57)
5 mg | 2.96 (1.81) | 2.50 (0.50-4.00) | 6.16 (1.85)
10 mg | 7.88 (4.54) | 1.50 (0.50-3.50) | 15.2 (5.52)

A slight increase in dose proportionality on mean Cmax and AUC(0-12) of dronabinol was observed with increasing dose over the dose range studied.

Metabolism: Dronabinol undergoes extensive first-pass hepatic metabolism, primarily by microsomal hydroxylation, yielding both active and inactive metabolites. Dronabinol and its principal active metabolite, 11-OH-delta-9-THC, are present in approximately equal concentrations in plasma. Concentrations of both parent drug and metabolite peak at approximately 0.5 to 4 hours after oral dosing and decline over several days. Values for clearance average about 0.2 L/kg-hr, but are highly variable due to the complexity of cannabinoid distribution.

Elimination: Dronabinol and its biotransformation products are excreted in both feces and urine. Biliary excretion is the major route of elimination with about half of a radio-labeled oral dose being recovered from the feces within 72 hours as contrasted with 10 to 15% recovered from urine. Less than 5% of an oral dose is recovered unchanged in the feces.

Following single dose administration, low levels of dronabinol metabolites have been detected for more than 5 weeks in the urine and feces.

In a study of dronabinol capsules involving AIDS patients, urinary cannabinoid/creatinine concentration ratios were studied bi-weekly over a six week period. The urinary cannabinoid/creatinine ratio was closely correlated with dose. No increase in the cannabinoid/creatinine ratio was observed after the first two weeks of treatment, indicating that steady-state cannabinoid levels had been reached. This conclusion is consistent with predictions based on the observed terminal half-life of dronabinol.

Special Populations: The pharmacokinetic profile of dronabinol capsules has not been investigated in either pediatric or geriatric patients.

CLINICAL TRAILS

Appetite Stimulation: The appetite stimulant effect of dronabinol capsules in the treatment of AIDS-related anorexia associated with weight loss was studied in a randomized, double-blind, placebo-controlled study involving 139 patients. The initial dosage of dronabinol capsules in all patients was 5 mg/day, administered in doses of 2.5 mg one hour before lunch and one hour before supper. In pilot studies, early morning administration of dronabinol capsules appeared to have been associated with an increased frequency of adverse experiences, as compared to dosing later in the day. The effect of dronabinol capsules on appetite, weight, mood, and nausea was measured at scheduled intervals during the six-week treatment period. Side effects (feeling high, dizziness, confusion, somnolence) occurred in 13 of 72 patients (18%) at this dosage level and the dosage was reduced to 2.5 mg/day, administered as a single dose at supper or bedtime.

Of the 112 patients that completed at least 2 visits in the randomized, double-blind, placebo-controlled study, 99 patients had appetite data at 4-weeks (50 received dronabinol and 49 received placebo) and 91 patients had appetite data at 6-weeks (46 received dronabinol and 45 received placebo). A statistically significant difference between dronabinol capsules and placebo was seen in appetite as measured by the visual analog scale at weeks 4 and 6 (see figure). Trends toward improved body weight and mood, and decreases in nausea were also seen.

After completing the 6-week study, patients were allowed to continue treatment with dronabinol capsules in an open-label study, in which there was a sustained improvement in appetite.

.

Antiemetic: Dronabinol treatment of chemotherapy-induced emesis was evaluated in 454 patients with cancer, who received a total of 750 courses of treatment of various malignancies. The antiemetic efficacy of dronabinol was greatest in patients receiving cytotoxic therapy with MOPP for Hodgkin’s and non-Hodgkin’s lymphomas. Dronabinol capsules dosages ranged from 2.5 mg/day to 40 mg/day, administered in equally divided doses every four to six hours (four times daily). As indicated in the following table, escalating the dronabinol dose above 7 mg/m^2 increased the frequency of adverse experiences, with no additional antiemetic benefit.

Dronabinol Dose: Response Frequency and Adverse Experiences*
(N = 750 treatment courses)

Dronabinol Dose | Response Frequency (%) |  |  | Adverse Events Frequency (%)
 | Complete | Partial | Poor | None | Nondysphoric | Dysphoric
<7 mg/m^2 | 36 | 32 | 32 | 23 | 65 | 12
>7 mg/m^2 | 33 | 31 | 36 | 13 | 58 | 28
*Nondysphoric events consisted of drowsiness, tachycardia, etc.

Combination antiemetic therapy with dronabinol capsules and a phenothiazine (prochlorperazine) may result in synergistic or additive antiemetic effects and attenuate the toxicities associated with each of the agents.

INDIVIDUALIZATION OF DOSAGES

The pharmacologic effects of dronabinol are dose-related and subject to considerable interpatient variability. Therefore, dosage individualization is critical in achieving the maximum benefit of dronabinol treatment.

Appetite Stimulation: In the clinical trials, the majority of patients were treated with 5 mg/day dronabinol capsules, although the dosages ranged from 2.5 to 20 mg/day. For an adult:

1. Begin with 2.5 mg before lunch and 2.5 mg before supper. If CNS symptoms (feeling high, dizziness, confusion, somnolence) do occur, they usually resolve in 1 to 3 days with continued dosage.
2. If CNS symptoms are severe or persistent, reduce the dose to 2.5 mg before supper. If symptoms continue to be a problem, taking the single dose in the evening or at bedtime may reduce their severity.
3. When adverse effects are absent or minimal and further therapeutic effect is desired, increase the dose to 2.5 mg before lunch and 5 mg before supper or 5 and 5 mg. Although most patients respond to 2.5 mg twice daily, 10 mg twice daily has been tolerated in about half of the patients in appetite stimulation studies.

The pharmacologic effects of dronabinol capsules are reversible upon treatment cessation.

Antiemetic: Most patients respond to 5 mg three or four times daily. Dosage may be escalated during a chemotherapy cycle or at subsequent cycles, based upon initial results. Therapy should be initiated at the lowest recommended dosage and titrated to clinical response. Administration of dronabinol capsules with phenothiazines, such as prochlorperazine, has resulted in improved efficacy as compared to either drug alone, without additional toxicity.

Pediatrics: Dronabinol capsules are not recommended for AIDS-related anorexia in pediatric patients because it has not been studied in this population. The pediatric dosage for the treatment of chemotherapy-induced emesis is the same as in adults. Caution is recommended in prescribing dronabinol capsules for children because of the psychoactive effects.

Geriatrics: Caution is advised in prescribing dronabinol capsules in elderly patients because they may be more sensitive to the neurological, psychoactive and postural hypotensive effects of the drug. In general, dose selection for an elderly patient should be cautious, usually starting at the low end of the dosing range (See PRECAUTIONS.)

Dronabinol capsules should be used with caution when administered to elderly patients with dementia, who are at increased risk for falls as a result of their underlying disease state which may be exacerbated by the central nervous system effects of somnolence and dizziness associated with dronabinol capsules. These patients should be monitored closely and placed on fall precautions prior to initiating dronabinol therapy. In antiemetic studies, no difference in efficacy was apparent in patients >55 years old.

INDICATIONS AND USAGE

Dronabinol capsules are indicated for the treatment of:

1. anorexia associated with weight loss in patients with AIDS; and
2. nausea and vomiting associated with cancer chemotherapy in patients who have failed to respond adequately to conventional antiemetic treatments.

CONTRAINDICATIONS

Dronabinol capsules are contraindicated in any patient who has a known sensitivity to dronabinol or any of its ingredients. It contains cannabinoid and sesame oil and should never be used by patients allergic to these substances.

WARNINGS

Patients receiving treatment with dronabinol capsules should be specifically warned not to drive, operate machinery, or engage in any hazardous activity until it is established that they are able to tolerate the drug and to perform such tasks safely.

PRECAUTIONS

General:

The risk/benefit ratio of dronabinol use should be carefully evaluated in patients with the following medical conditions because of individual variation in response and tolerance to the effects of dronabinol.

Seizure and seizure-like activity have been reported in patients receiving dronabinol capsules during marketed use of the drug and in clinical trials. (See ADVERSE REACTIONS and OVERDOSAGE.) Dronabinol capsules should be used with caution in patients with a history of seizure disorder because dronabinol capsules may lower the seizure threshold. A causal relationship between dronabinol capsules and these events has not been established. Dronabinol capsules should be discontinued immediately in patients who develop seizures and medical attention should be sought immediately.

Dronabinol capsules should be used with caution in patients with cardiac disorders because of occasional hypotension, possible hypertension, syncope, or tachycardia (see CLINICAL PHARMACOLOGY).

Dronabinol capsules should be used with caution in patients with a history of substance abuse, including alcohol abuse or dependence, because they may be more prone to abuse dronabinol capsules as well. Multiple substance abuse is common and marijuana, which contains the same active compound, is a frequently abused substance.

Dronabinol capsules should be used with caution and careful psychiatric monitoring in patients with mania, depression, or schizophrenia because dronabinol capsules may exacerbate these illnesses.

Dronabinol capsules should be used with caution in patients receiving concomitant therapy with sedatives, hypnotics or other psychoactive drugs because of the potential for additive or synergistic CNS effects.

Dronabinol capsules should be used with caution in elderly patients because they may be more sensitive to the neurological, psychoactive, and postural hypotensive effects of the drug. (see INDIVIDUALIZATION OF DOSAGES.)

Dronabinol capsules should be used with caution in pregnant patients, nursing mothers, or pediatric patients because it has not been studied in these patient populations.

Information for Patients:

Patients receiving treatment with dronabinol capsules should be alerted to the potential for additive central nervous system depression if dronabinol capsules is used concomitantly with alcohol or other CNS depressants such as benzodiazepines and barbiturates.

Patients receiving treatment with dronabinol capsules should be specifically warned not to drive, operate machinery, or engage in any hazardous activity until it is established that they are able to tolerate the drug and to perform such tasks safely.

Patients using dronabinol capsules should be advised of possible changes in mood and other adverse behavioral effects of the drug so as to avoid panic in the event of such manifestations. Patients should remain under the supervision of a responsible adult during initial use of dronabinol capsules and following dosage adjustments.

Drug Interactions:

In studies involving patients with AIDS and/or cancer, dronabinol capsules have been co-administered with a variety of medications (e.g., cytotoxic agents, anti-infective agents, sedatives, or opioid analgesics) without resulting in any clinically significant drug/drug interactions. Although no drug/drug interactions were discovered during the clinical trials of dronabinol capsules, cannabinoids may interact with other medications through both metabolic and pharmacodynamic mechanisms. Dronabinol is highly protein bound to plasma proteins, and therefore, might displace other protein-bound drugs. Although this displacement has not been confirmed in vivo, practitioners should monitor patients for a change in dosage requirements when administering dronabinol to patients receiving other highly protein-bound drugs. Published reports of drug/drug interactions involving cannabinoids are summarized in the following table.

CONCOMITANT DRUG | CLINICAL EFFECT(S)
Amphetamines, cocaine, other sympathomimetic agents | Additive hypertension, tachycardia, possibly cardiotoxicity
Atropine, scopolamine, antihistamines, other anticholinergic agents | Additive or super-additive tachycardia, drowsiness
Amitriptyline, amoxapine, desipramine, other tricyclic antidepressants | Additive tachycardia, hypertension, drowsiness
Barbiturates, benzodiazepines, ethanol, lithium, opioids, buspirone, antihistamines, muscle relaxants, other CNS depressants | Additive drowsiness and CNS depression
Disulfiram | A reversible hypomanic reaction was reported in a 28 y/o man who smoked marijuana; confirmed by dechallenge and rechallenge
Fluoxetine | A 21 y/o female with depression and bulimia receiving 20 mg/day fluoxetine X 4 wks became hypomanic after smoking marijuana; symptoms resolved after 4 days
Antipyrine, barbiturates | Decreased clearance of these agents,presumably via competitive inhibition of metabolism
Theophylline | Increased theophylline metabolism reported with smoking of marijuana; effect similar to that following smoking tobacco

Carcinogenesis, Mutagenesis, Impairment of Fertility:

Carcinogenicity studies in mice and rats have been conducted under the U.S. National Toxicology Program (NTP). In the 2-year carcinogenicity study in rats, there was no evidence of carcinogenicity at doses up to 50 mg/kg/day, about 20 times the maximum recommended human dose on a body surface area basis. In the 2-year carcinogenicity study in mice, treatment with dronabinol at 125 mg/kg/day, about 25 times the maximum recommended human dose on a body surface area basis, produced thyroid follicular cell adenoma in both male and female mice but not at 250 or 500 mg/kg/day.

Dronabinol was not genotoxic in the Ames tests, the in vitro chromosomal aberration test in Chinese hamster ovary cells, and the in vivo mouse micronucleus test. It, however, produced a weak positive response in a sister chromatid exchange test in Chinese hamster ovary cells.

In a long-term study (77 days) in rats, oral administration of dronabinol at doses of 30 to 150 mg/m^2, equivalent to 0.3 to 1.5 times maximum recommended human dose (MRHD) of 90 mg/m^2/day in cancer patients or 2 to 10 times MRHD of 15 mg/m^2/day in AIDS patients, reduced ventral prostate, seminal vesicle and epididymal weights and caused a decrease in seminal fluid volume. Decreases in spermatogenesis, number of developing germ cells, and number of Leydig cells in the testis were also observed. However, sperm count, mating success and testosterone levels were not affected. The significance of these animal findings in humans is not known.

Pregnancy:

Pregnancy Category C. Reproduction studies with dronabinol have been performed in mice at 15 to 450 mg/m^2, equivalent to 0.2 to 5 times maximum recommended human dose (MRHD) of 90 mg/m^2/day in cancer patients or 1 to 30 times MRHD of 15 mg/m^2/day in AIDS patients, and in rats at 74 to 295 mg/m^2 (equivalent to 0.8 to 3 times MRHD of 90 mg/m^2 in cancer patients or 5 to 20 times MRHD of 15 mg/m^2/day in AIDS patients). These studies have revealed no evidence of teratogenicity due to dronabinol. At these dosages in mice and rats, dronabinol decreased maternal weight gain and number of viable pups and increased fetal mortality and early resorptions. Such effects were dose dependent and less apparent at lower doses which produced less maternal toxicity. There are no adequate and well-controlled studies in pregnant women. Dronabinol should be used only if the potential benefit justifies the potential risk to the fetus.

Nursing Mothers:

Use of dronabinol capsules is not recommended in nursing mothers since, in addition to the secretion of HIV virus in breast milk, dronabinol is concentrated in and secreted in human breast milk and is absorbed by the nursing baby.

Geriatric Use:

Clinical studies of dronabinol capsules in AIDS and cancer patients did not include the sufficient numbers of subjects aged 65 and over to determine whether they respond differently from younger subjects. Other reported clinical experience has not identified differences in responses between the elderly and younger patients. In general, dose selection for an elderly patient should be cautious usually starting at the low end of the dosing range, reflecting the greater frequency of falls, decreased hepatic, renal, or cardiac function, increased sensitivity to psychoactive effects and of concomitant disease or other drug therapy.

ADVERSE REACTIONS

Adverse experiences information summarized in the tables below was derived from well-controlled clinical trials conducted in the U.S. and U.S. territories involving 474 patients exposed to dronabinol capsules. Studies of AIDS-related weight loss included 157 patients receiving dronabinol at a dose of 2.5 mg twice daily and 67 receiving placebo. Studies of different durations were combined by considering the first occurrence of events during the first 28 days. Studies of nausea and vomiting related to cancer chemotherapy included 317 patients receiving dronabinol and 68 receiving placebo.

A cannabinoid dose-related “high” (easy laughing, elation and heightened awareness) has been reported by patients receiving dronabinol capsules in both the antiemetic (24%) and the lower dose appetite stimulant clinical trials (8%). (see CLINICAL TRIALS).

The most frequently reported adverse experiences in patients with AIDS during placebo-controlled clinical trials involved the CNS and were reported by 33% of patients receiving dronabinol capsules. About 25% of patients reported a minor CNS adverse event during the first 2 weeks and about 4% reported such an event each week for the next 6 weeks thereafter.

PROBABLY CAUSALLY RELATED: Incidence greater than 1%.

Rates derived from clinical trials in AIDS-related anorexia (N=157) and chemotherapy-related nausea (N=317). Rates were generally higher in the anti-emetic use (given in parentheses).

Body as a whole: Asthenia.

Cardiovascular: Palpitations, tachycardia, vasodilation/facial flush.

Digestive: Abdominal pain*, nausea*, vomiting*.

Nervous system: (Amnesia), anxiety/nervousness, (ataxia), confusion, depersonalization, dizziness*, euphoria*, (hallucination), paranoid reaction*, somnolence*, thinking abnormal*.

*Incidence of events 3% to 10%

PROBABLY CAUSALLY RELATED: Incidence less than 1%.

Event rates derived from clinical trials in AIDS-related anorexia (N=157) and chemotherapy-related nausea (N=317).

Cardiovascular: Conjunctivitis*, hypotension*.

Digestive: Diarrhea*, fecal incontinence.

Musculoskeletal: Myalgias.

Nervous system: Depression, nightmares, speech difficulties, tinnitus.

Skin and Appendages: Flushing*.

Special senses: Vision difficulties.

*Incidence of events 0.3% to 1%

CAUSAL RELATIONSHIP UNKNOWN: Incidence less than 1%.

The clinical significance of the association of these events with dronabinol capsules treatment is unknown, but they are reported as alerting information for the clinician.

Body as a whole: Chills, headache, malaise.

Digestive: Anorexia, hepatic enzyme elevation.

Respiratory: Cough, rhinitis, sinusitis.

Skin and Appendages: Sweating

Postmarketing Experience

Seizure and seizure-like activity have been reported in patients receiving dronabinol capsules during marketed use of the drug and in clinical trials. (see PRECAUTIONS and OVERDOSAGE.) Reports of fatigue have also been received. A causal relationship between dronabinol capsules and these events has not been established.

DRUG ABUSE AND DEPENDENCE

Dronabinol is one of the psychoactive compounds present in cannabis, and is abusable and controlled [Schedule III (CIII)] under the Controlled Substances Act. Both psychological and physiological dependence have been noted in healthy individuals receiving dronabinol, but addiction is uncommon and has only been seen after prolonged high dose administration.

Chronic abuse of cannabis has been associated with decrements in motivation, cognition, judgment, and perception. The etiology of these impairments is unknown, but may be associated with the complex process of addiction rather than an isolated effect of the drug. No such decrements in psychological, social or neurological status have been associated with the administration of dronabinol capsules for therapeutic purposes.

In an open-label study in patients with AIDS who received dronabinol capsules for up to five months, no abuse, diversion or systematic change in personality or social functioning were observed despite the inclusion of a substantial number of patients with a past history of drug abuse.

An abstinence syndrome has been reported after the abrupt discontinuation of dronabinol in volunteers receiving dosages of 210 mg/day for 12 to 16 consecutive days. Within 12 hours after discontinuation, these volunteers manifested symptoms such as irritability, insomnia, and restlessness. By approximately 24 hours post-dronabinol discontinuation, withdrawal symptoms intensified to include “hot flashes”, sweating, rhinorrhea, loose stools, hiccoughs and anorexia.

These withdrawal symptoms gradually dissipated over the next 48 hours. Electroencephalographic changes consistent with the effects of drug withdrawal (hyperexcitation) were recorded in patients after abrupt dechallenge. Patients also complained of disturbed sleep for several weeks after discontinuing therapy with high dosages of dronabinol.

OVERDOSAGE

Signs and symptoms following MILD dronabinol intoxication include drowsiness, euphoria, heightened sensory awareness, altered time perception, reddened conjunctiva, dry mouth and tachycardia; following MODERATE intoxication include memory impairment, depersonalization, mood alteration, urinary retention, and reduced bowel motility; and following SEVERE intoxication include decreased motor coordination, lethargy, slurred speech, and postural hypotension. Apprehensive patients may experience panic reactions and seizures may occur in patients with existing seizure disorders.

The estimated lethal human dose of intravenous dronabinol is 30 mg/kg (2100 mg/70 kg). Significant CNS symptoms in antiemetic studies followed oral doses of 0.4 mg/kg (28 mg/70 kg) of dronabinol capsules.

Management: A potentially serious oral ingestion, if recent, should be managed with gut decontamination. In unconscious patients with a secure airway, instill activated charcoal (30 to 100 g in adults, 1 to 2 g/kg in infants) via a nasogastric tube. A saline cathartic or sorbitol may be added to the first dose of activated charcoal. Patients experiencing depressive, hallucinatory or psychotic reactions should be placed in a quiet area and offered reassurance. Benzodiazepines (5 to 10 mg diazepam po) may be used for treatment of extreme agitation. Hypotension usually responds to Trendelenburg position and IV fluids. Pressors are rarely required.

DOSAGE AND ADMINISTRATION

Appetite Stimulation: Initially, 2.5 mg dronabinol capsules should be administered orally twice daily (b.i.d.), before lunch and supper. For patients unable to tolerate this 5 mg/day dosage of dronabinol capsules, the dosage can be reduced to 2.5 mg/day, administered as a single dose in the evening or at bedtime. If clinically indicated and in the absence of significant adverse effects, the dosage may be gradually increased to a maximum of 20 mg/day dronabinol capsules, administered in divided oral doses. Caution should be exercised in escalating the dosage of dronabinol capsules because of the increased frequency of dose-related adverse experiences at higher dosages. (see PRECAUTIONS.)

Antiemetic: Dronabinol Capsules are best administered at an initial dose of 5 mg/m^2, given 1 to 3 hours prior to the administration of chemotherapy, then every 2 to 4 hours after chemotherapy is given, for a total of 4 to 6 doses/day. Should the 5 mg/m^2 dose prove to be ineffective, and in the absence of significant side effects, the dose may be escalated by 2.5 mg/m^2 increments to a maximum of 15 mg/m^2 per dose. Caution should be exercised in dose escalation, however, as the incidence of disturbing psychiatric symptoms increases significantly at maximum dose (see PRECAUTIONS).

STORAGE CONDITIONS

Dronabinol Capsules, USP should be packaged in a well-closed container and stored in a refrigerator, 2° to 8°C (36° to 46°F).
Protect from freezing.

HOW SUPPLIED

Dronabinol Capsules (dronabinol solution in sesame oil in soft gelatin capsules)

5 mg - opaque brown, oblong softgel capsules printed “PAR 868” in black ink.

NDC 54868-5929-0 Bottle of 60 capsules
Manufactured by:
Pharmaceutics International, Inc.
Hunt Valley, MD 21031

Manufactured for:
Par Pharmaceutical Companies, Inc.
Spring Valley, NY 10977

Revised: 11/2011

OS867-15-17-02

302850-0B

Additional barcode labeling by:
Physicians Total Care, Inc.
Tulsa, Oklahoma 74146

PACKAGE LABEL.PRINCIPAL DISPLAY PANEL

Bottle of 60 Capsules NDC 54868-5929-0

CIII Rx Only